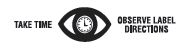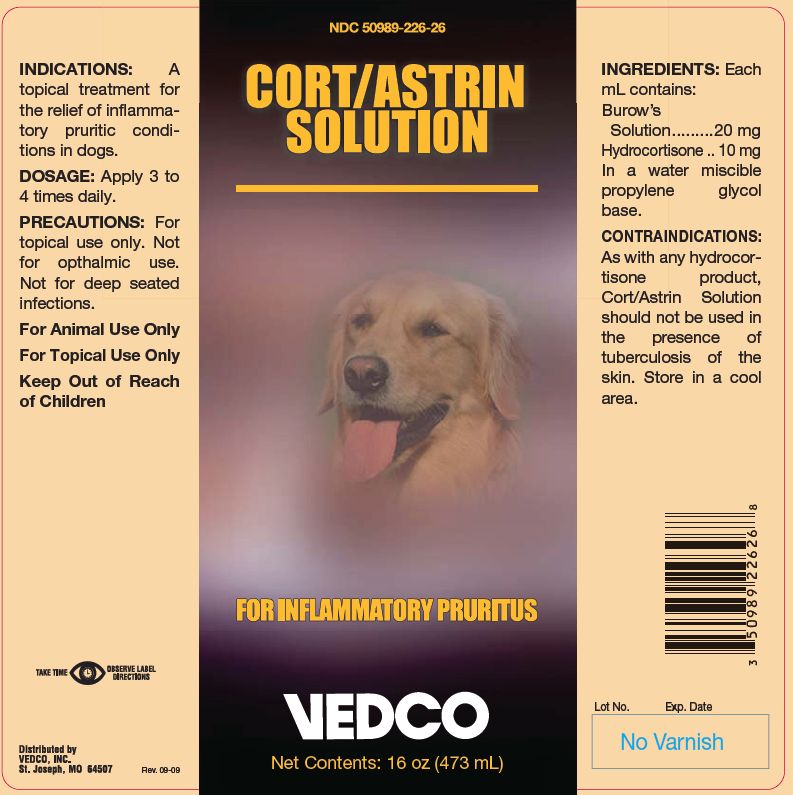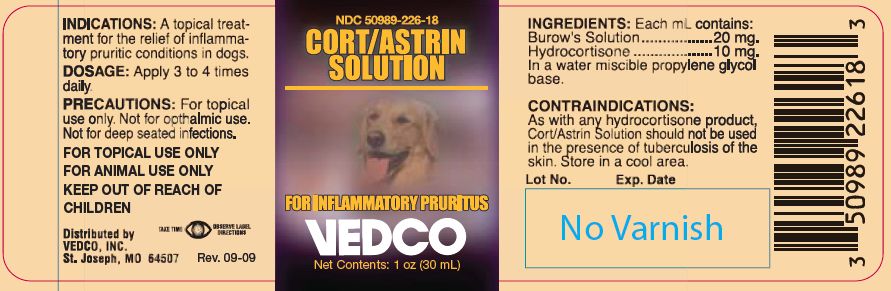 DRUG LABEL: CORT ASTRIN
NDC: 50989-226 | Form: SOLUTION
Manufacturer: Vedco, Inc.
Category: animal | Type: OTC ANIMAL DRUG LABEL
Date: 20221115

ACTIVE INGREDIENTS: HYDROCORTISONE 10.2 mg/1 mL; ALUMINUM ACETATE .73 mg/1 mL; ACETIC ACID 0.624 mg/1 mL

CORT/ASTRIN SOLUTION

PURPOSE

FOR INFLAMMATORY PRURITUS

INDICATIONS:

A topical treatment for the relief of inflammatory pruritic conditions in dogs.

DOSAGE:

Apply 3 to 4 times daily.

PRECAUTIONS:

For topical use only. Not for opthalmic use. Not for deep seated infections.

KEEP OUT OF REACH OF CHILDREN

For Animal Use Only

For Topical Use Only

Keep Out of Reach of Children

INGREDIENTS:

Each mL contains:
Burow’s Solution.........20 mg
Hydrocortisone .. 10 mg

INACTIVE INGREDIENT

In a water miscible propylene glycol base.

CONTRAINDICATIONS:

As with any hydrocortisone product, Cort/Astrin Solution should not be used in the presence of tuberculosis of the skin. Store in a cool area.

Net Contents:

1 oz (30 mL)

16 oz (473 mL)